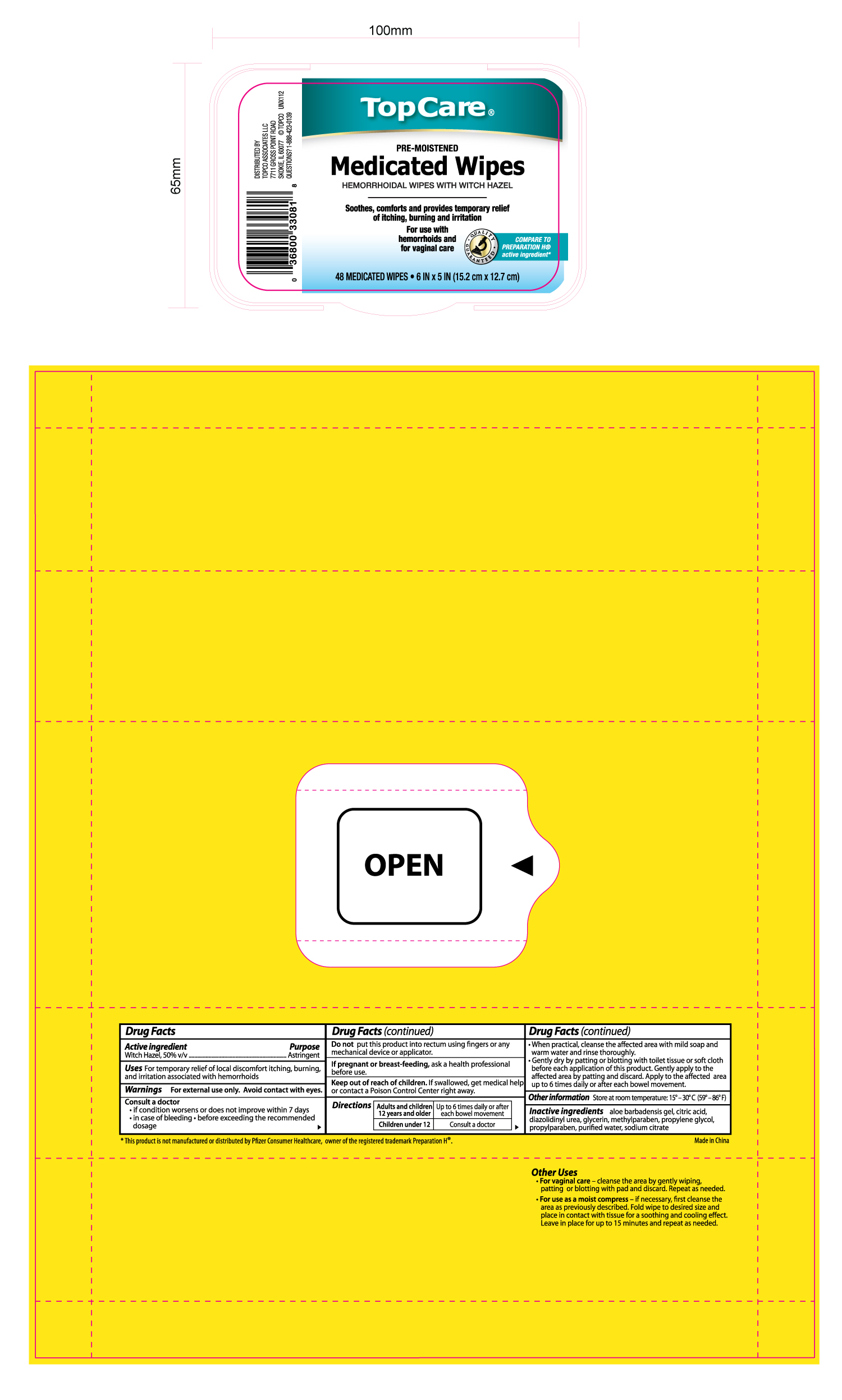 DRUG LABEL: TOPCARE MEDICATED WIPES
NDC: 36800-330 | Form: CLOTH
Manufacturer: TOPCO ASSOCIATES LLC
Category: otc | Type: HUMAN OTC DRUG LABEL
Date: 20120301

ACTIVE INGREDIENTS: WITCH HAZEL 0.5 mL/1 mL
INACTIVE INGREDIENTS: CITRIC ACID MONOHYDRATE; DIAZOLIDINYL UREA; GLYCERIN; METHYLPARABEN; PROPYLENE GLYCOL; PROPYLPARABEN; SODIUM CITRATE; WATER

Drug Facts

Active ingredient Purpose

Witch Hazel, 50% v/v...........................................................Astringent

Uses

For temporary relief of local discomfort itching, burning, and irritation associated with hermorrhoids

Warnings

For external use only. Avoid contact with eyes.

Consult a doctor

- if condition worsens or does not improve within 7 days
- in case of bleeding
- before exceeding the recommended dosage

DO NOT USE

Do not put this product into rectum using fingers or any mechanical device or applicator.

PREGNANCY OR BREAST FEEDING

If pregnant or breast-feeding, ask a health professional before use.

Keep out of reach of children.

If swallowed, get medical help or contact a Poison Control Center right away.

Directions

Adults and children 12 years and older- Up to 6 times daily or after each bowel movement

Children under 12- Consult a doctor

When practical, cleanse the affected area with mild soap and warm water and rinse thoroughly.

Gently dry by patting or blotting with toilet tissue or soft cloth before each application of this product.

Gently apply to the affected area by patting and discard. Apply to the affected area up to 6 times daily or after each bowel movement.

STORAGE AND HANDLING

Store at room temperature: 15o-30oC (59o-86oF)

Inactive ingredients

aloe barbadensis gel, citric acid, diazolidinyl urea, glycerin, methylparaben, propylene glycol, propylparaben, purified water, sodium citrate

DOSAGE AND ADMINISTRATION

DISTRIBUTED BY

TOPCO ASSOCIATES LLC

7711 GROSS POINT ROAD

SKOKIE, IL 60077

QUESTIONS? 1-888-423-0139

Made in China

PACKAGE LABEL

Enter section text here